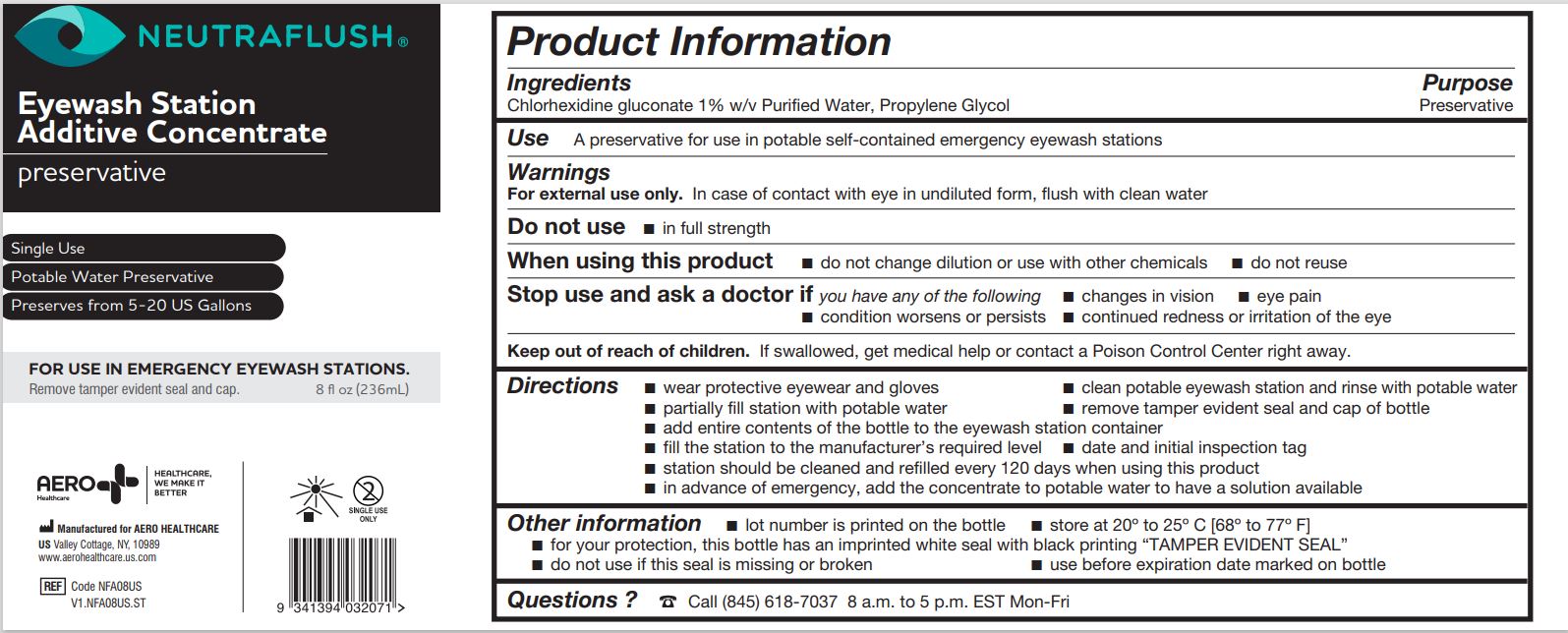 DRUG LABEL: Neutraflush
NDC: 55305-134 | Form: LIQUID
Manufacturer: Aero Healthcare
Category: otc | Type: HUMAN OTC DRUG LABEL
Date: 20240904

ACTIVE INGREDIENTS: PROPYLENE GLYCOL 280 kg/2800 L; CHLORHEXIDINE GLUCONATE 145.6 kg/2800 L
INACTIVE INGREDIENTS: WATER 2374.4 L/2800 L

Neutraflush Eyewash Station Additive Concentrate

Ingredients

Chlorhexidine gluconate 1% w/v Purified Water, Propylene Glycol

Purpose

Preservative

Use

A preservative for use in potable self-contained emergency eyewash stations

Warnings

For external use only. In case of contact with eye in undiluted form, flush with clean water

Do not use

- in full strength

When using this product

- do not change dilution or use with other chemicals
- do not reuse

Stop use and ask a doctor if you have any of the following

- changes in vision
- eye pain
- condition worsens or persists
- continued redness or irritations of the eye

Keep out of reach of children. If swallowed, get medical help or contact a Poison Control Center right away.

Directions

- wear protective eyewear and gloves
- clean potable eyewash station and rinse with potable water
- partially fill station with potable water
- remove tamper evident seal and cap of bottle
- add entire contents of the bottle to the eyewash station container
- fill the station to the manufacturer's required level
- date and initial inspection tag
- station should be cleaned and refilled every 120 days when using this product
- in advance of emergency, add the concentrate to potable water to have solution available

Other Information

- lot number is printed on the bottle
- store at 20º to 25º C [68º to 77º F]
- for your protection, this bottle has an imprinted white seal with black printing "TAMPER EVIDENT SEAL"
- do not use if this seal is missing or broken
- use before expiration date marked on bottle

Questions?

Call (845) 618-7037 8 a.m. to 5 p.m. EST Mon-Fri

Inactive Ingredients

Purified Water

Principle Display Panel

Eyewash Station Additive Concentrate

preservative

- Single Use
- Potable Water Preservative
- Preserves from 5-20 US Gallons

FOR USE IN EMERGENCY EYEWASH STATIONS

Remove tamper evident seal and cap.

8 fl oz (236mL)

Manufactured for Aero Healthcare

US Valley Cottage, NY, 10989